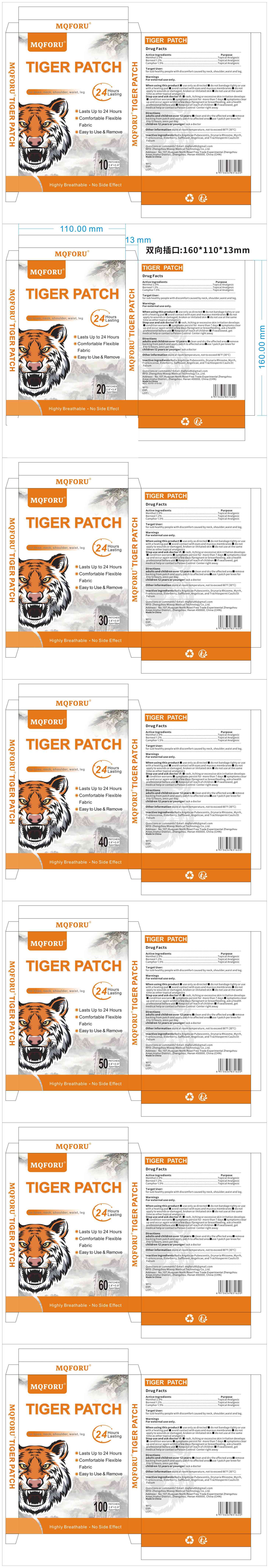 DRUG LABEL: Mqforu Pain Patch
NDC: 83781-010 | Form: PATCH
Manufacturer: Zhengzhou Miaoqi Medical Technology Co., Ltd.
Category: otc | Type: HUMAN OTC DRUG LABEL
Date: 20250422

ACTIVE INGREDIENTS: MENTHOL 2 g/100 1; CAMPHOR (SYNTHETIC) 1.5 g/100 1; BORNEOL 1.2 g/100 1
INACTIVE INGREDIENTS: ANGELICA BISERRATA WHOLE; FRANKINCENSE; MYRRH; ANGELICIN; TRACHELOSPERMUM JASMINOIDES STEM; EUROPEAN ELDERBERRY; DRYNARIA FORTUNEI ROOT; SAFFLOWER

83781-010 Updete V2

Active Ingredient

Menthol 2.0%

Borneol 1.2%

Camphor 1.5%

Purpose

Topical Analgesic

Use

Target User: for sub healthy people with discomfort caused by neck, shoulder,waist and leg.

Warnings

For external use only.

Do not use

When using this product

■ use only as directed

■ do not bandage tighty or use with a heating pad

■ avoid contact with eyes and mucous membranes

■ do not apply to wounds or damaged, broken or imitated skin

■ do not use at the same time as other topical analgesics

When Using

When using this product

■ use only as directed

■ do not bandage tighty or use with a heating pad

■ avoid contact with eyes and mucous membranes

■ do not apply to wounds or damaged, broken or imitated skin

■ do not use at the same time as other topical analgesics

Stop Use

Stop use and ask doctor if:

■ rash, itching or excessive skin irritation develops

■ condition worsens

■ symptoms persist for more than 7 days

■ symptoms clear up and occur again within a few days If pregnant or breastfeeding, ask a health professional before use

■ Keep out of reach of children

■ If swallowed, get medical help or contact a Poison Control Center right away

Ask Doctor

Stop use and ask doctor if:

■ rash, itching or excessive skin irritation develops

■ condition worsens

■ symptoms persist for more than 7 days

■ symptoms clear up and occur again within a few days If pregnant or breastfeeding, ask a health professional before use

■ Keep out of reach of children

■ If swallowed, get medical help or contact a Poison Control Center right away

Keep Out Of Reach Of Children

Directions

adults and children over 12 years:

■clean and dry the affected area

■remove backing from patch and apply patch to affected area

■use 1 patch per knee for 8 to 12 hours, once per day
children 12 years or younger: ask a doctor

Other information

store at room temperature, not to exceed 86°F (30°C)

Inactive ingredients

Radix Angelicae Pubescentis, Drynaria Rhizome, Myrrh, Frankincense, Elderberry, Safflower, Angelicae, and Trachlospermi Caulis Et Folium

Questions

Questions or comments?

Email: mqforu86@gmail.com